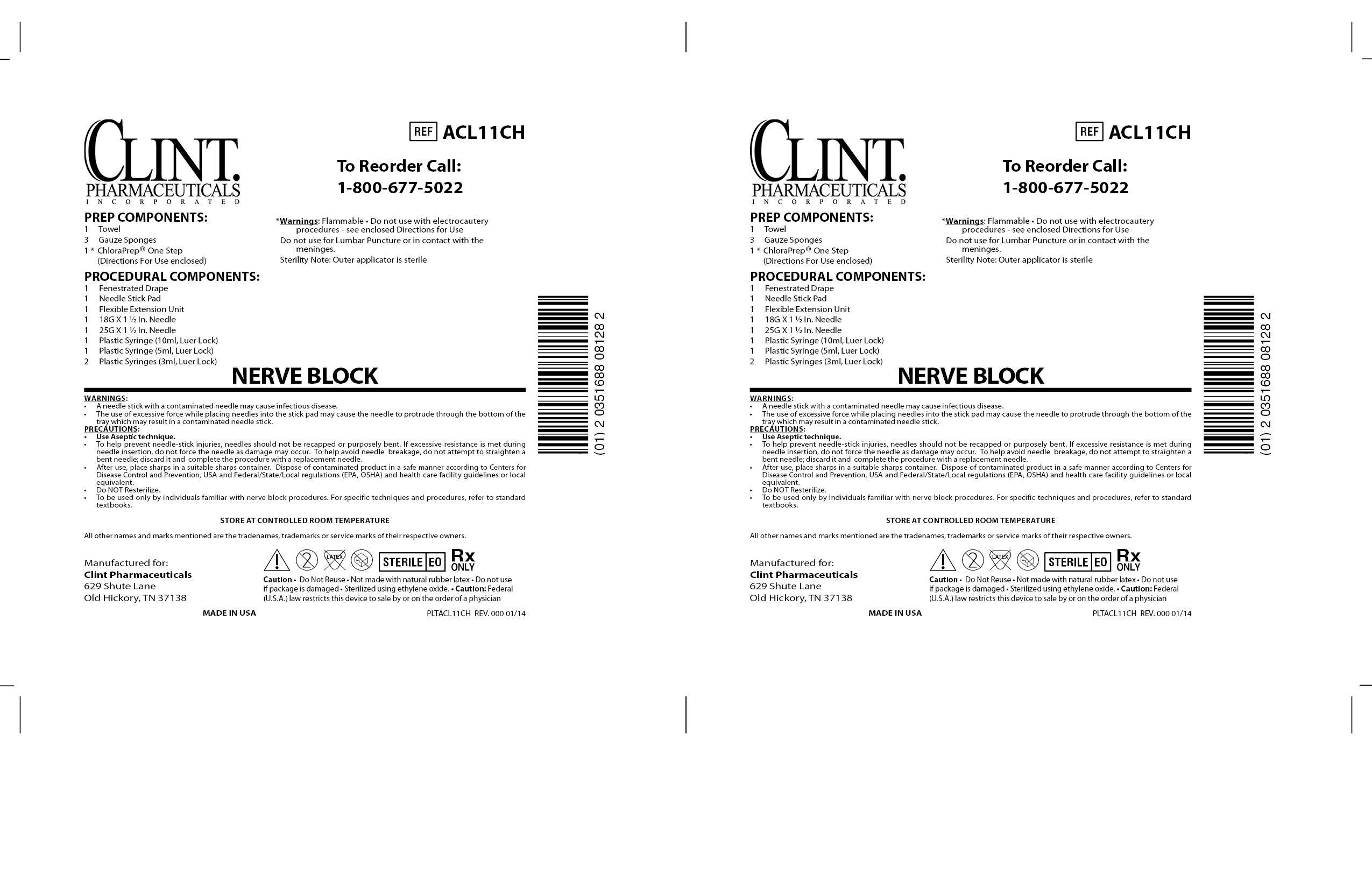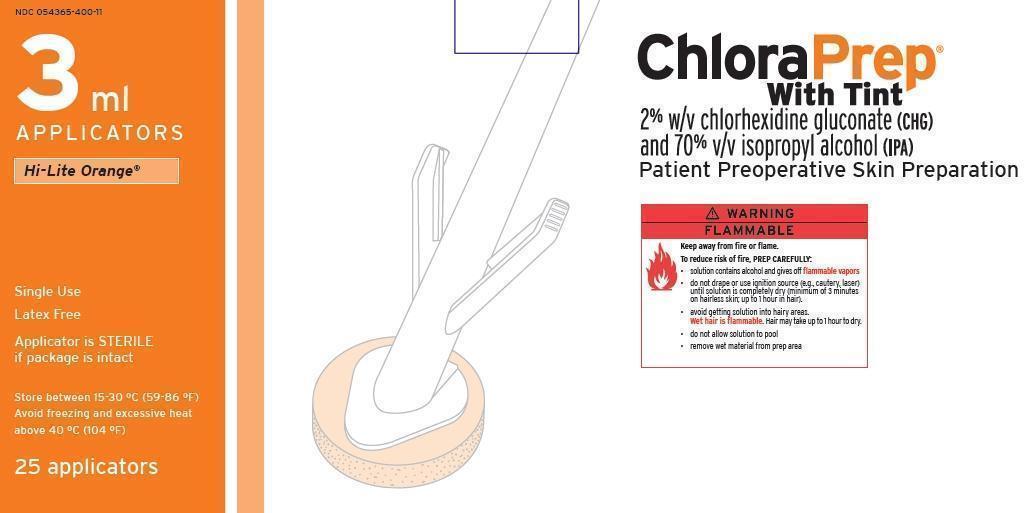 DRUG LABEL: ACL11CH NERVE BLOCK             
NDC: 55553-482 | Form: KIT | Route: TOPICAL
Manufacturer: Smiths Medical ASD, Inc.
Category: other | Type: MEDICAL DEVICE
Date: 20140414

ACTIVE INGREDIENTS: CHLORHEXIDINE GLUCONATE 20 mg/1 mL; ISOPROPYL ALCOHOL 0.70 mL/1 mL
INACTIVE INGREDIENTS: WATER

ACTIVE INGREDIENT

CHLORAPREP ONE-STEP (chlorhexidine gluconate and isopropyl aclohol) solution
[CareFusion 213 LLC]

Active ingredients
Chlorhexidine gluconate 2% w/v
Isopropyl alcohol 70% v/v

Purposes
Antiseptic
Antiseptic
Use
for the preparation of the patient's skin prior to surgery. Helps to reduce bacteria that potentially can cause skin infection.

Warnings
For external use only. Flammable, keep away from fire or flame.
To reduce the risk of fire, PREP CAREFULLY:
•
solution contains alcohol and gives off flammable vapors
•
avoid getting solution into hairy areas. Hair may take up to 1 hour to dry. Wet hair is flammable.
•
do not drape or use ignition source (e.g., cautery, laser) until solution is completely dry (minimum of 3 minutes on hairless skin; up to 1 hour in hair).
•
do not allow solution to pool
•
remove wet materials from prep area

Do not use
•
on patients with known allergies to chlorhexidine gluconate or isopropyl alcohol
•
for lumbar puncture or in contact with the meninges
•
on open skin wounds or as a general skin cleanser

When using this product
•
keep out of eyes, ears, and mouth. May cause serious or permanent injury if permitted to enter and remain. If contact occurs, rinse with cold water right away and contact a doctor.

Stop use and ask a doctor if
•
irritation, sensitization, or allergic reaction occurs. These may be signs of a serious condition.

Keep out of reach of children.
If swallowed, get medical help or contact a Poison Control Center right away.

Directions
•
use with care in premature infants or infants under 2 months of age. These products may cause irritation or chemical burns.
•
use in a well ventilated area
•
maximal treatment area for one applicator is approximately 4 in. x 5 in. (130 cm2)
•
remove applicator from package; do not touch sponge
•
hold the applicator with the sponge down. Pinch wings only once to activate the ampule and release the antiseptic.
•
wet the sponge by pressing and releasing the sponge against the treatment area until liquid is visible on the skin
•
completely wet the treatment area with antiseptic
•
dry surgical sites (e.g., abdomen or arm): use gentle repeated back-and-forth strokes for 30 seconds
•
moist surgical sites (e.g., inguinal fold): use gentle repeated back-and-forth strokes for 2 minutes
•
allow the solution to completely dry (minimum of 3 minutes on hairless skin; up to 1 hour in hair). Do not blot or wipe away.
•
discard the applicator after a single use along with any portion of the solution not required to cover the prep area. It is not necessary to use the entire amount available.

Other information
•
store between 15-30 °C (59-86 °F)
•
avoid freezing and excessive heat above 40 °C (104 °F)
•
the tint will slowly fade from the skin. Soap and water, or alcohol may be used to remove the tint if desired.

Inactive ingredients
•
FD&C yellow #6 dye
•
USP purified water

Package Label Display Panel